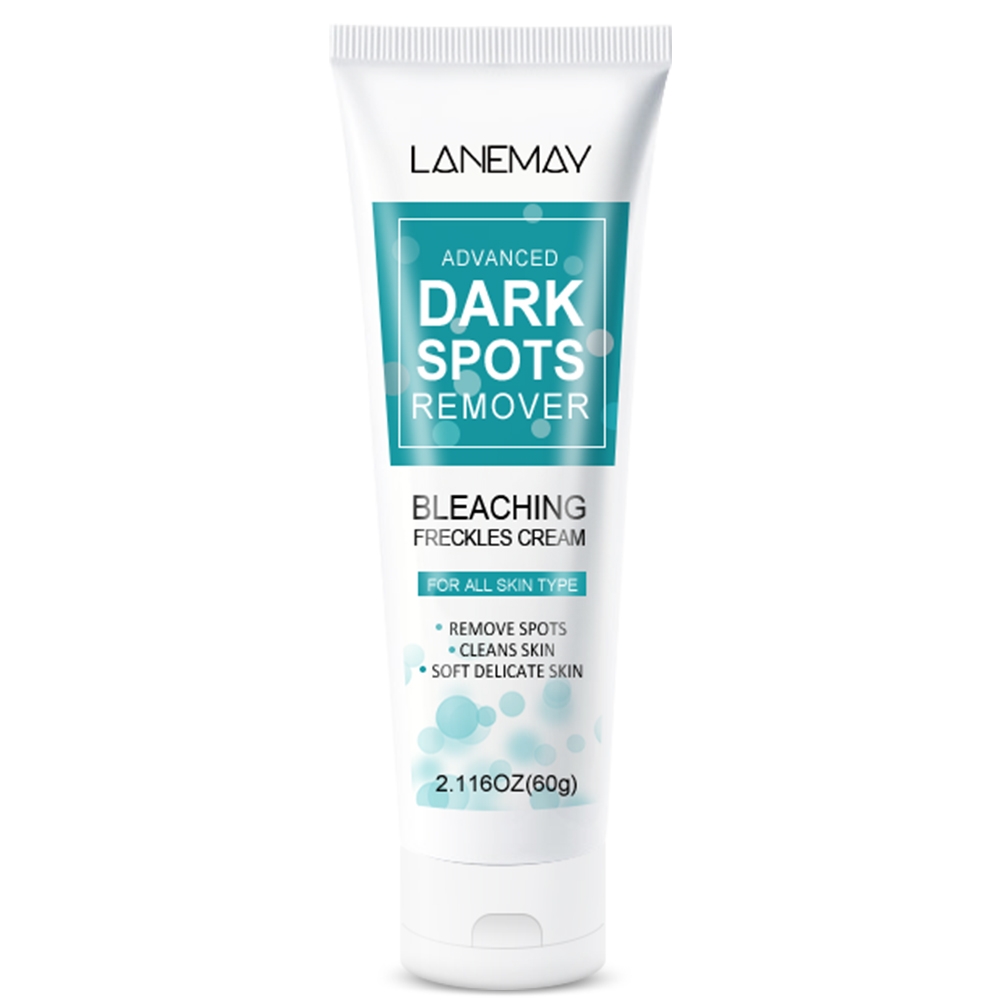 DRUG LABEL: Dark Spot Remover
NDC: 84025-216 | Form: CREAM
Manufacturer: Guangzhou Yanxi Biotechnology Co., Ltd
Category: otc | Type: HUMAN OTC DRUG LABEL
Date: 20241016

ACTIVE INGREDIENTS: GLYCERIN 3 mg/60 g; CETYL ETHYLHEXANOATE 2 mg/60 g
INACTIVE INGREDIENTS: WATER

DOSAGE AND ADMINISTRATION

Apply a small amount of the serum to targeted dark spots or your entire face.Gently massage it in and allow it to absorb.

WARNINGS

keep out of children

INACTIVE INGREDIENT

Aqua

INDICATIONS AND USAGE

For daily skin care

keep out of children

PURPOSE

Cleans skin and remove spots.